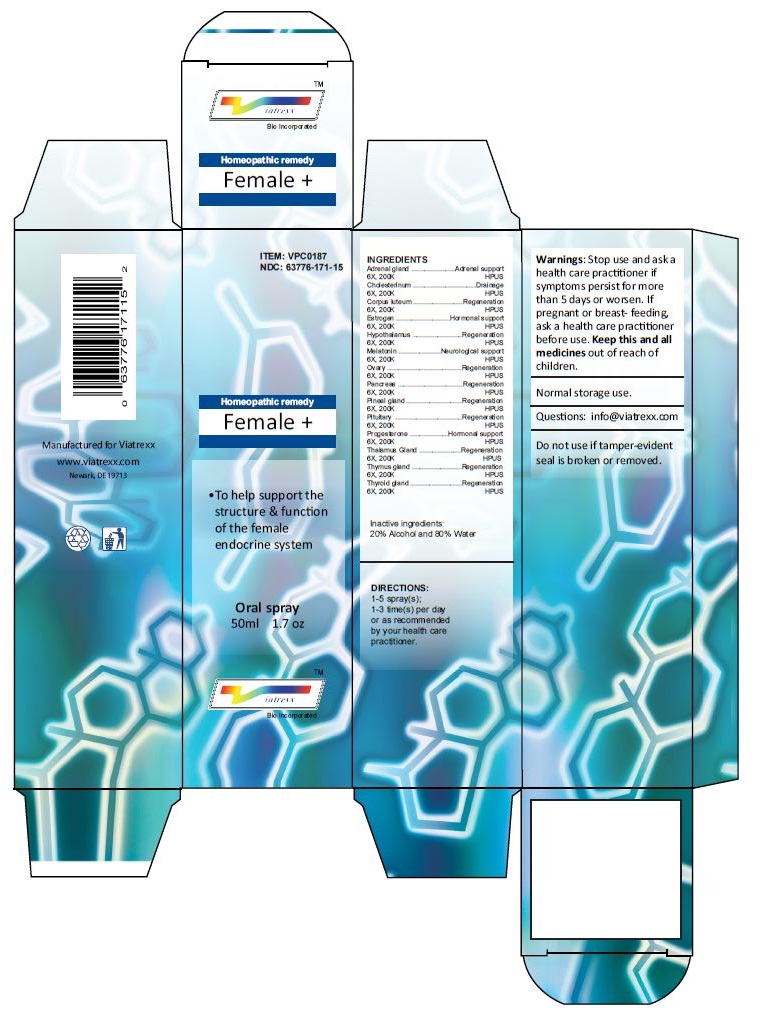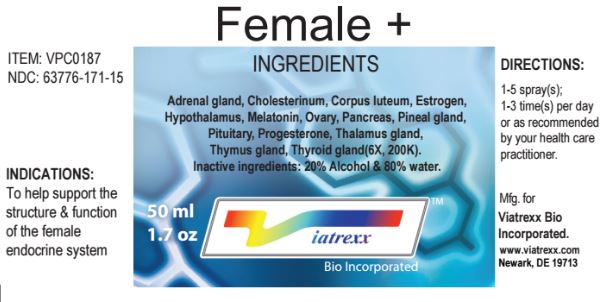 DRUG LABEL: Female
NDC: 63776-171 | Form: SPRAY
Manufacturer: VIATREXX BIO INCORPORATED
Category: homeopathic | Type: HUMAN OTC DRUG LABEL
Date: 20221130

ACTIVE INGREDIENTS: BOS TAURUS ADRENAL GLAND 200 [kp_C]/1 mL; SUS SCROFA ADRENAL GLAND 200 [kp_C]/1 mL; CHOLESTEROL 200 [kp_C]/1 mL; SUS SCROFA CORPUS LUTEUM 200 [kp_C]/1 mL; ESTROGENS, ESTERIFIED 200 [kp_C]/1 mL; BOS TAURUS HYPOTHALAMUS 200 [kp_C]/1 mL; SUS SCROFA HYPOTHALAMUS 200 [kp_C]/1 mL; MELATONIN 200 [kp_C]/1 mL; BOS TAURUS OVARY 200 [kp_C]/1 mL; SUS SCROFA OVARY 200 [kp_C]/1 mL; BOS TAURUS PANCREAS 200 [kp_C]/1 mL; SUS SCROFA PANCREAS 200 [kp_C]/1 mL; BOS TAURUS PINEAL GLAND 200 [kp_C]/1 mL; SUS SCROFA PINEAL GLAND 200 [kp_C]/1 mL; BOS TAURUS PITUITARY GLAND 200 [kp_C]/1 mL; SUS SCROFA PITUITARY GLAND 200 [kp_C]/1 mL; PROGESTERONE 200 [kp_C]/1 mL; SUS SCROFA THALAMUS 200 [kp_C]/1 mL; BOS TAURUS THYMUS 200 [kp_C]/1 mL; SUS SCROFA THYMUS 200 [kp_C]/1 mL; THYROID, BOVINE 200 [kp_C]/1 mL; THYROID, PORCINE 200 [kp_C]/1 mL
INACTIVE INGREDIENTS: ALCOHOL; WATER

Female +

Active Ingredients

Adrenal gland 6X 200K, Cholesterinum 6X 200K, Corpus luteum 6X 200K, Estrogen 6X 200K, Hypothalamus 6X 200K, Melatonin 6X 200K, Ovary 6X 200K, Pancreas 6X 200K, Pineal gland 6X 200K, Pituitary 6X 200K, Progesterone 6X 200K, Thalamus Gland 6X 200K, Thymus gland 6X 200K, Thyroid gland 6X 200K

Purpose

Adrenal gland | Adrenal support
Cholesterinum | Drainage
Corpus luteum | Regeneration
Estrogen | Hormonal support
Hypothalamus | Regeneration
Melatonin | Neurological support
Ovary | Regeneration
Pancreas | Regeneration
Pineal gland | Regeneration
Pituitary | Regeneration
Progesterone | Hormonal support
Thalamus Gland | Regeneration
Thymus gland | Regeneration
Thyroid gland | Regeneration

Uses

To help support the structure & function of the female endocrine system

Warnings

Stop use and ask a health care practitioner if symptoms persist for more than 5 days or worsen. If pregnant or breastfeeding, ask a health care practitioner before use.

Dosage

1-3 spray(s); 1-3 time(s) per day or as recommended by your healthcare practitioner.

KEEP OUT OF REACH OF CHILDREN

Keep this and all medicines out of reach of children.

Other Ingredients

Alcohol and Water

Other Information

Normal storage use.
Do not use if tamper-evident seal is broken or removed.

Questions

info@viatrexx.com

Principal Display Panel

ITEM: VPC0187
NDC 63776-171-15
Homeopathic remedy
Female +
• To help support the structure & function of the female endocrine system
Oral spray
50ml 1.7 oz
Viatrexx™ Bio Incorporated
Manufactured by Viatrexx
www.viatrexx.com
Newark, DE 19713

Female +
50 mL
1.7 oz
Viatrexx™ Bio Incorporated
ITEM: VPC0187
NDC: 63776-171-15
INDICATIONS:
To help support the structure & function of the female endocrine system
DIRECTIONS:
1-5 spray(s); 1-3 time(s) per day or as recommended by your health care practitioner.
Mfg. for
Viatrexx Bio Incorporated.
www.viatrexx.com
Newark, DE 19713